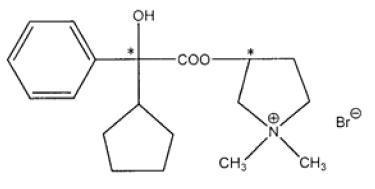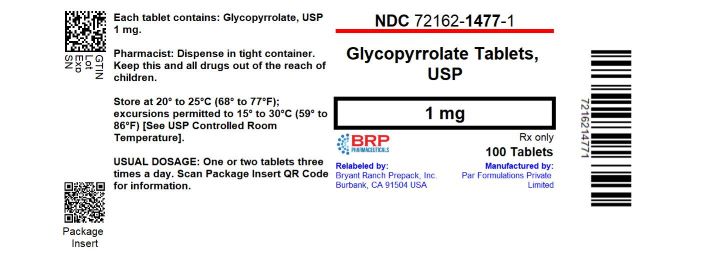 DRUG LABEL: Glycopyrrolate
NDC: 72162-1477 | Form: TABLET
Manufacturer: Bryant Ranch Prepack
Category: prescription | Type: HUMAN PRESCRIPTION DRUG LABEL
Date: 20250106

ACTIVE INGREDIENTS: GLYCOPYRROLATE 1 mg/1 1
INACTIVE INGREDIENTS: DIBASIC CALCIUM PHOSPHATE DIHYDRATE; LACTOSE, UNSPECIFIED FORM; MAGNESIUM STEARATE; POVIDONE, UNSPECIFIED; SODIUM STARCH GLYCOLATE TYPE A POTATO

GLYCOPYRROLATE TABLETS, USP
Rx only

DESCRIPTION

Glycopyrrolate tablets contain the synthetic anticholinergic glycopyrrolate. Glycopyrrolate is a quaternary ammonium compound with the following chemical name:

3-[(cyclopentylhydroxyphenylacetyl)oxy]-1,1-dimethylpyrrolidinium bromide. Its empirical formula is C19H28BrNO3, its molecular weight is 398.33, and its structural formula is:

Each 1 mg tablet contains: Glycopyrrolate, USP 1mg

Each 2 mg tablet contains: Glycopyrrolate, USP 2mg

Inactive Ingredients: Dibasic Calcium Phosphate, Lactose, Magnesium Stearate, Povidone, Sodium Starch Glycolate.

ACTIONS

Glycopyrrolate, like other anticholinergic (antimuscarinic) agents, inhibits the action of acetylcholine on structures innervated by postganglionic cholinergic nerves and on smooth muscles that respond to acetylcholine but lack cholinergic innervation. These peripheral cholinergic receptors are present in the autonomic effector cells of smooth muscle, cardiac muscle, the sino-atrial node, the atrioventricular node, exocrine glands, and, to a limited degree, in the autonomic ganglia. Thus, it diminishes the volume and free acidity of gastric secretions and controls excessive pharyngeal, tracheal, and bronchial secretions.

Glycopyrrolate antagonizes muscarinic symptoms (e.g., bronchorrhea, bronchospasm, bradycardia, and intestinal hypermotility) induced by cholinergic drugs such as the anticholinesterases.

The highly polar quaternary ammonium group of glycopyrrolate limits its passage across lipid membranes, such as the blood-brain barrier, in contrast to atropine sulfate and scopolamine hydrobromide, which are non-polar tertiary amines which penetrate lipid barriers easily.

INDICATIONS

For use as adjunctive therapy in the treatment of peptic ulcer.

CONTRAINDICATIONS

Glaucoma; obstructive uropathy (for example, bladder neck obstruction due to prostatic hypertrophy); obstructive disease of the gastrointestinal tract (as in achalasia, pyloroduodenal stenosis, etc.); paralytic ileus; intestinal atony of the elderly or debilitated patient; unstable cardiovascular status in acute hemorrhage; severe ulcerative colitis; toxic megacolon complicating ulcerative colitis; myasthenia gravis. Glycopyrrolate tablets are contraindicated in those patients with a hypersensitivity to glycopyrrolate.

WARNINGS

In the presence of a high environmental temperature, heat prostration (fever and heat stroke due to decreased sweating) can occur with use of glycopyrrolate.

Diarrhea may be an early symptom of incomplete intestinal obstruction, especially in patients with ileostomyor colostomy. In this instance treatment with this drug would be inappropriate and possibly harmful.

Glycopyrrolate may produce drowsiness or blurred vision. In this event, the patient should be warned not to engage in activities requiring mental alertness such as operating a motor vehicle or other machinery, or performing hazardous work while taking this drug.

Theoretically, with overdosage, a curare-like action may occur, i.e., neuro-muscular blockade leading to muscular weakness and possible paralysis.

Pregnancy

The safety of this drug during pregnancy has not been established. The use of any drug during pregnancy requires that the potential benefits of the drug be weighed against possible hazards to mother and child. Reproduction studies in rats revealed no teratogenic effects from glycopyrrolate; however, the potent anticholinergic action of this agent resulted in diminished rates of conception and of survival at weaning, in a dose-related manner. Other studies in dogs suggest that this may be due to diminished seminal secretion which is evident at high doses of glycopyrrolate. Information on possible adverse effects in the pregnant female is limited to uncontrolled data derived from marketing experience. Such experience has revealed no reports of teratogenic or other fetus-damaging potential. No controlled studies to establish the safety of the drug in pregnancy have been performed.

Nursing Mothers

It is not known whether this drug is excreted in human milk. As a general rule, nursing should not be undertaken while a patient is on a drug since many drugs are excreted in human milk.

Pediatric Use

Since there is no adequate experience in pediatric patients who have received this drug, safety and efficacy in pediatric patients have not been established.

PRECAUTIONS

Use glycopyrrolate with caution in the elderly and in all patients with:

- Autonomic neuropathy.
- Hepatic or renal disease.
- Ulcerative colitis-large doses may suppress intestinal motility to the point of producing a paralytic ileus and for this reason may precipitate or aggravate “toxic megacolon,” a serious complication of the disease.
- Hyperthyroidism, coronary heart disease, congestive heart failure, cardiac tachyarrhythmias, tachycardia, hypertension and prostatic hypertrophy.
- Hiatal hernia associated with reflux esophagitis, since anticholinergic drugs may aggravate this condition.

ADVERSE REACTIONS

Anticholinergics produce certain effects, most of which are extensions of their fundamental pharmacological actions. Adverse reactions to anticholinergics in general may include xerostomia; decreased sweating; urinary hesitancy and retention; blurred vision; tachycardia; palpitations; dilatation of the pupil; cycloplegia; increased ocular tension; loss of taste; headaches; nervousness; mental confusion; drowsiness; weakness; dizziness; insomnia; nausea; vomiting; constipation; bloated feeling; impotence; suppression of lactation; severe allergic reaction or drug idiosyncrasies including anaphylaxis, urticaria and other dermal manifestations.

Glycopyrrolate is chemically a quaternary ammonium compound; hence, its passage across lipid membranes, such as the blood-brain barrier, is limited in contrast to atropine sulfate and scopolamine hydrobromide. For this reason the occurrence of CNS related side effects is lower, in comparison to their incidence following administration of anticholinergics which are chemically tertiary amines that can cross this barrier readily.

OVERDOSAGE

The symptoms of overdosage of glycopyrrolate are peripheral in nature rather than central.

1. To guard against further absorption of the drug-use gastric lavage, cathartics and/or enemas.
2. To combat peripheral anticholinergic effects (residual mydriasis, dry mouth, etc.)-utilize a quaternary ammonium anticholinesterase, such as neostigmine methylsulfate.
3. To combat hypotension-use pressor amines (norepinephrine, metaraminol) i.v.; and supportive care.
4. To combat respiratory depression-administer oxygen; utilize a respiratory stimulant such as Dopram® i.v.; artificial respiration.

DOSAGE AND ADMINISTRATION

The dosage of glycopyrrolate should be adjusted to the needs of the individual patient to assure symptomatic control with a minimum of adverse reactions. The presently recommended maximum daily dosage of glycopyrrolate is 8 mg.

Glycopyrrolate Tablets 1 mg. The recommended initial dosage of glycopyrrolate for adults is one tablet three times daily (in the morning, early afternoon, and at bedtime). Some patients may require two tablets at bedtime to assure overnight control of symptoms. For maintenance, a dosage of one tablet twice a day is frequently adequate.

Glycopyrrolate Tablets 2 mg. The recommended dosage of glycopyrrolate for adults is one tablet two or three times daily at equally spaced intervals.

Glycopyrrolate tablets are not recommended for use in pediatric patients under the age of 12 years.

DRUG INTERACTIONS

There are no known drug interactions.

HOW SUPPLIED

Glycopyrrolate tablets 1 mg are bisected, compressed white, round tablets debossed “K” above the bisect and “400” below the bisect on one side of the tablet, and plain on the other side.

NDC: 72162-1477-1: 100 Tablets in a BOTTLE

Store at 20°-25°C (68°-77°F); excursions permitted to 15°-30°C (59°-86°F) [see USP Controlled Room Temperature].

Dispense in tight container.

Repackaged/Relabeled by:
Bryant Ranch Prepack, Inc. Burbank, CA 91504

PACKAGE LABEL

Glycopyrrolate 1 mg Tablet, #100